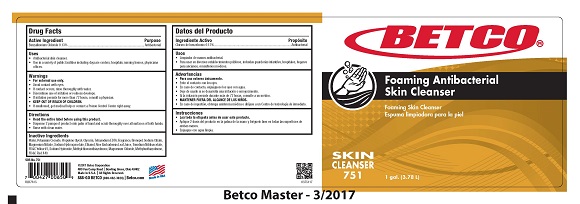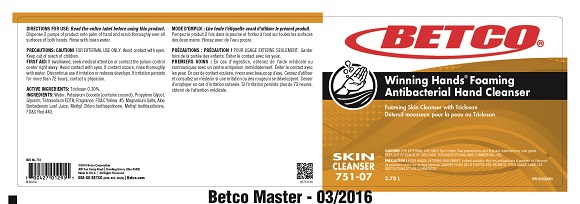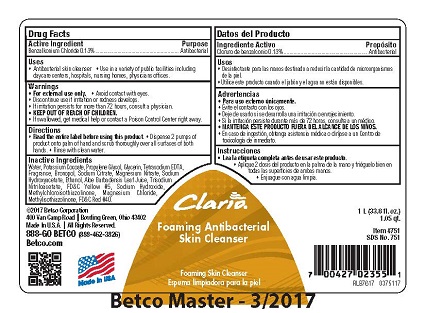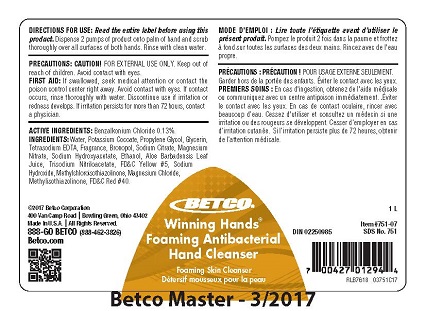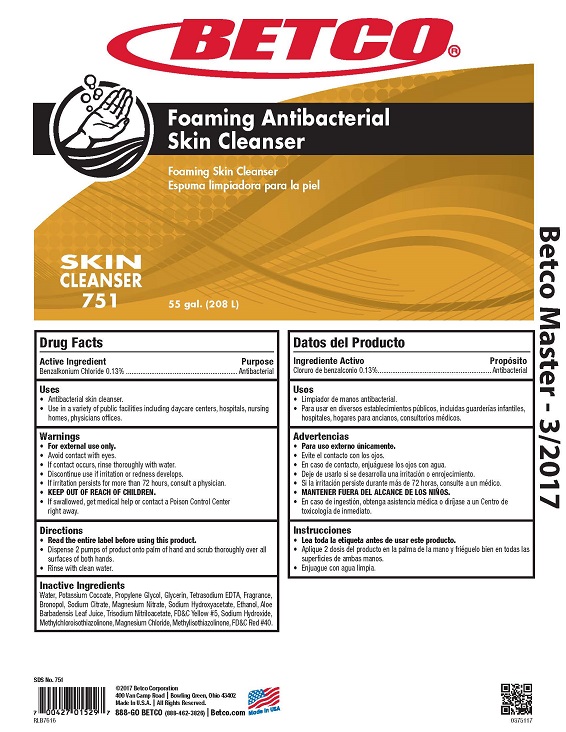 DRUG LABEL: Winning Hands Foaming Antibacterial
NDC: 65601-754 | Form: SOAP
Manufacturer: Betco Corporation, Ltd.
Category: otc | Type: HUMAN OTC DRUG LABEL
Date: 20190214

ACTIVE INGREDIENTS: BENZALKONIUM CHLORIDE 13 mg/1.0 mL
INACTIVE INGREDIENTS: WATER; POTASSIUM COCOATE; PROPYLENE GLYCOL; GLYCERIN; DITETRACYCLINE TETRASODIUM EDETATE; BRONOPOL; SODIUM CITRATE; MAGNESIUM NITRATE; SODIUM GLYCOLATE; ALCOHOL; ALOE; TRISODIUM NITRILOTRIACETATE; FD&C YELLOW NO. 5; SODIUM HYDROXIDE; METHYLCHLOROISOTHIAZOLINONE; MAGNESIUM CHLORIDE; METHYLISOTHIAZOLINONE; FD&C RED NO. 40

Winning Hands Foaming Antibacterial

Winning Hands Foaming Antibacterial

Active Ingredient

Benzalkonium Chloride 0.13%

Winning Hands Foaming Antibacterial

Uses

- Antibacterial hand cleaner.
- Use in a variet of public facilities including daycare centers, hospitals, nursing homes, physicians offices.

Winning Hands Foaming Antibacterial

Warnings

- For external use only.
- Avoid contact with eyes.
- Children under the age of 6 should be supervised by an adult when using this product.
- Discontinue use is irritation or redness develops.
- If irritation persists for more than 72 hours, consult a physician.
- KEEP OUT OF REACH OF CHILDREN.
- If swallowed, get medical help or contact a Poison Control Center right away.

Winning Hands Foaming Antibacterial

Directions

- Read the entire label before using this product.
- Dispense 2 pumps of product onto palm of hand and scrub thoroughly over all surfaces of both hands.
- Rinse with clean water.

Winning Hands Foaming Antibacterial

Inactive Ingredients

Water, Potassium Cocoate, Propylene Glycol, Glycerin, Tetrasodium EDTA, Fragrance, Bronopol, Sodium Citrate,
Magnesium Nitrate, Sodium Hydroxyacetate, Ethanol, Aloe Barbadensis Leaf Juice, Trisodium Nitriloacetate,
FD&C Yellow #5, Sodium Hydroxide, Methylchloroisothiazolinone, Magnesium Chloride, Methylisothiazolinone,
FD&C Red #40.

Winning Hands Foaming Antibacterial

Betco.com
©2017 Betco Corporation
400 Van Camp Road Bowling Green, Ohio 43402
Made In U.S.A. All Rights Reserved.

888-GO BETCO (888-462-3826) Betco.com

Winning Hands Foaming Antibacterial

Purpose

Antibacterial

Winning Hands Foaming Antibacterial

KEEP OUT OF REACH OF CHILDREN

Winning Hands Foaming Antibacterial

75155-00

Foaming Skin Cleanser with Triclosan

NET CONTENTS: 55 gallons (U.S./E.U.) 208 L